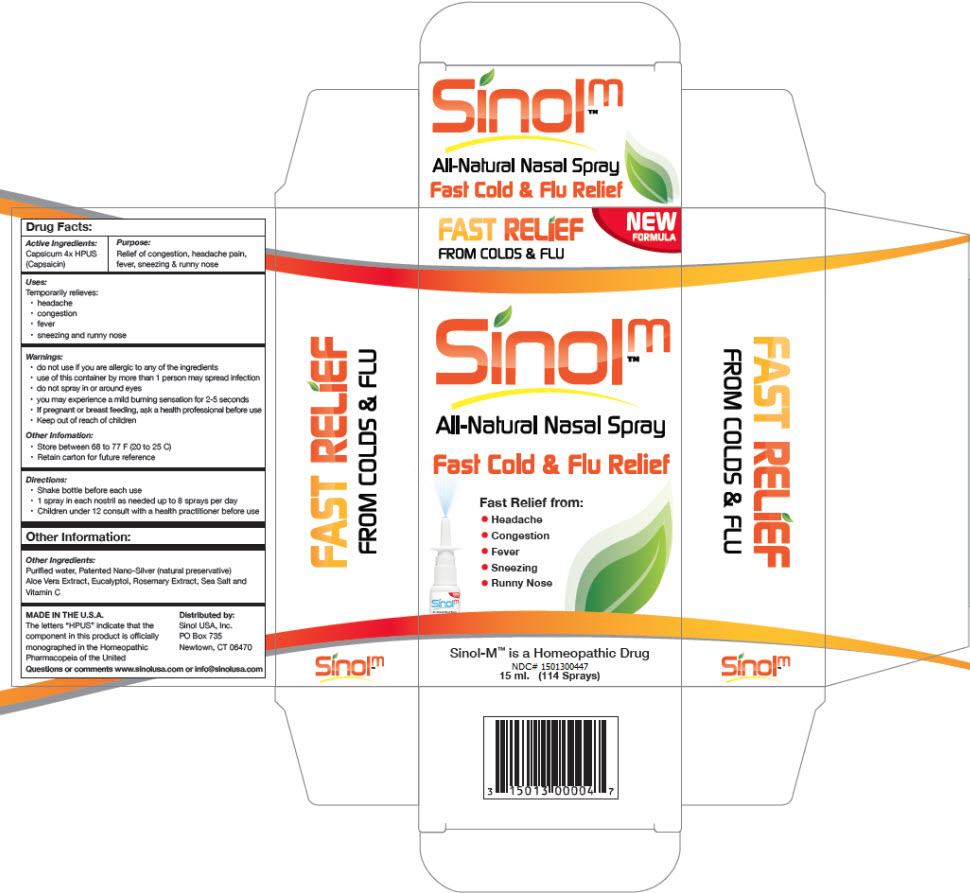 DRUG LABEL: SinolM Cold and Flu 

NDC: 15013-004 | Form: SPRAY
Manufacturer: Sinol USA, Inc.
Category: homeopathic | Type: HUMAN OTC DRUG LABEL
Date: 20250129

ACTIVE INGREDIENTS: CAPSICUM 4 [hp_X]/0.263 mL
INACTIVE INGREDIENTS: WATER; SILVER; ALOE; EUCALYPTOL; ROSEMARY; SEA SALT; ASCORBIC ACID

SinolM™ Cold and Flu
All-Natural Nasal Spray

Drug Facts:

Active Ingredients

Capsicum 4x HPUS (Capsaicin)

Purpose

Relief of congestion, headache pain, fever, sneezing & runny nose

Uses

Temporarily relieves:

- headache
- congestion
- fever
- sneezing and runny nose

Warnings

- do not use if you are allergic to any of the ingredients

WHEN USING

- use of this container by more than 1 person may spread infection
- do not spray in or around eyes
- you may experience a mild burning sensation for 2-5 seconds

PREGNANCY OR BREAST FEEDING

- If pregnant or breast feeding, ask a health professional before use

- Keep out of reach of children

Other Information

- Store between 68 to 77 F (20 to 25 C)
- Retain carton for future reference

Directions

- Shake bottle before each use
- 1 spray in each nostril as needed up to 8 sprays per day
- Children under 12 consult with a health practitioner before use

Other Information

Other Ingredients

Purified water, Patented Nano-Silver (natural preservative) Aloe Vera Extract, Eucalyptol, Rosemary Extract, Sea Salt and Vitamin C

Questions or comments

www.sinolusa.com or info@sinolusa.com

Distributed by:
Sinol USA, Inc.
PO Box 735
Newtown, CT 06470

PRINCIPAL DISPLAY PANEL - 15 ml Bottle Carton

FAST RELIEF
FROM COLDS & FLU

NEW
FORMULA

Sinolm™

All-Natural Nasal Spray

Fast Cold & Flu Relief

Fast Relief from:

- Headache
- Congestion
- Fever
- Sneezing
- Runny Nose

Sinol-M™ is a Homeopathic Drug
NDC# 1501300447
15 ml. (114 Sprays)